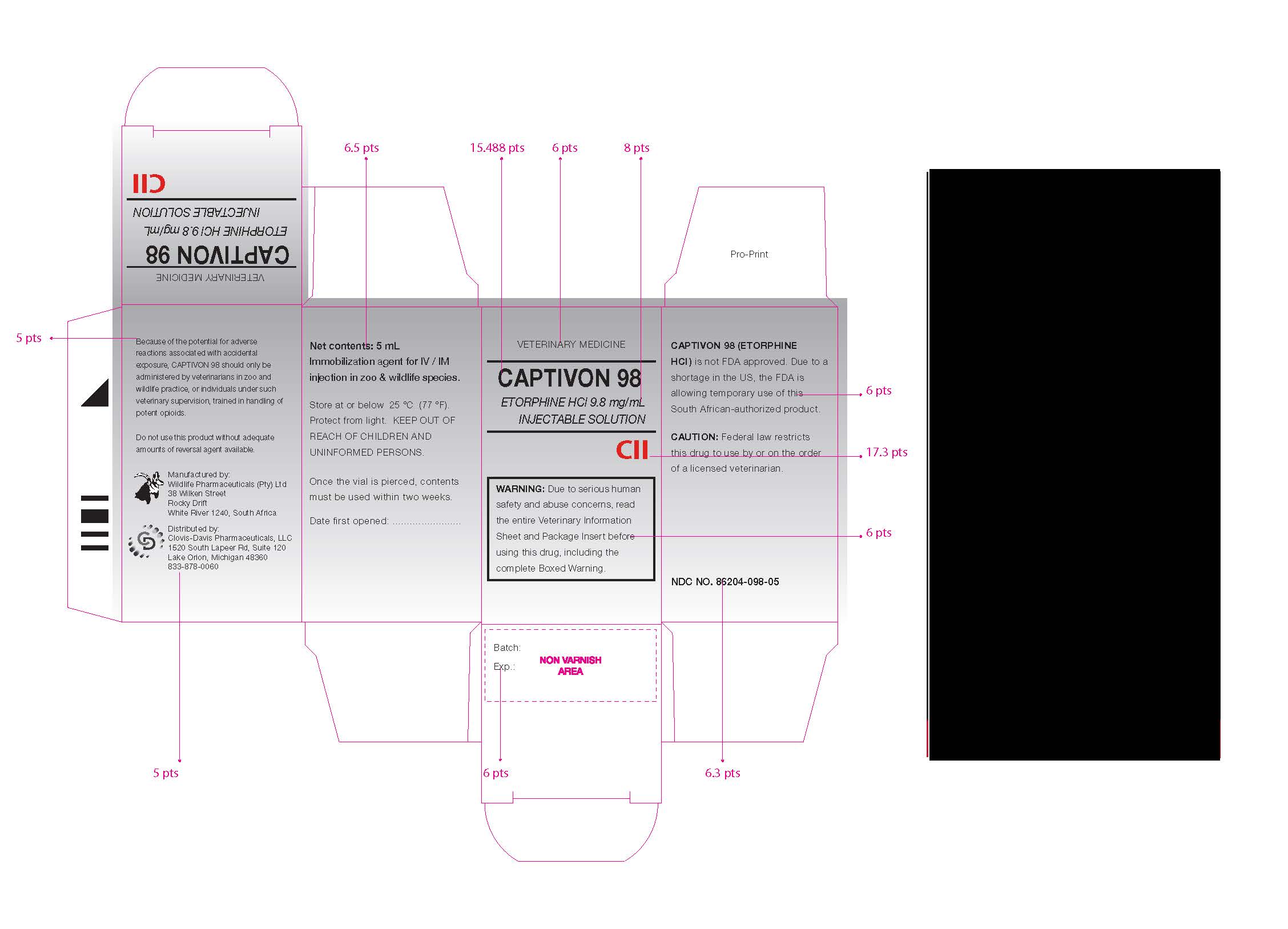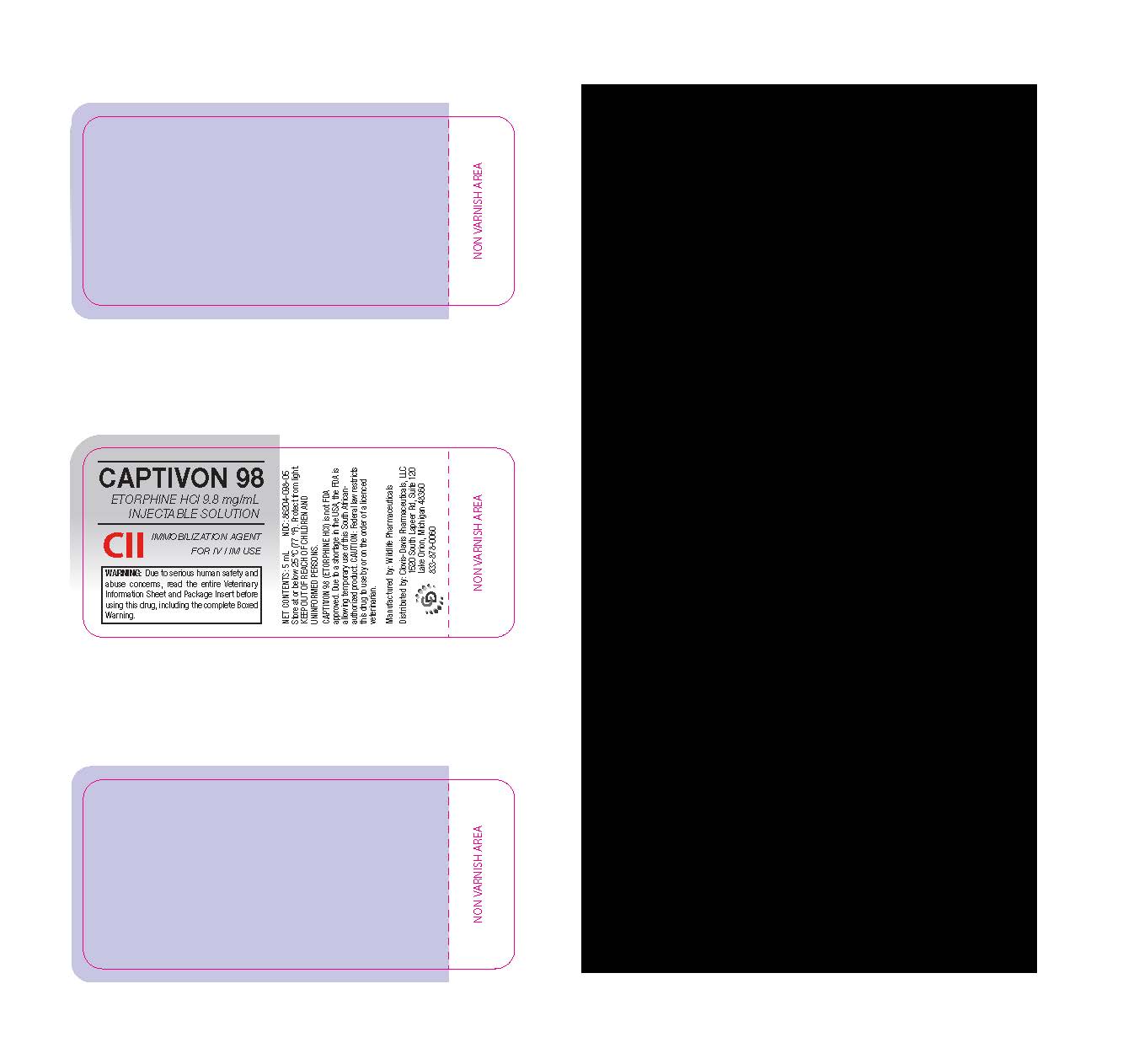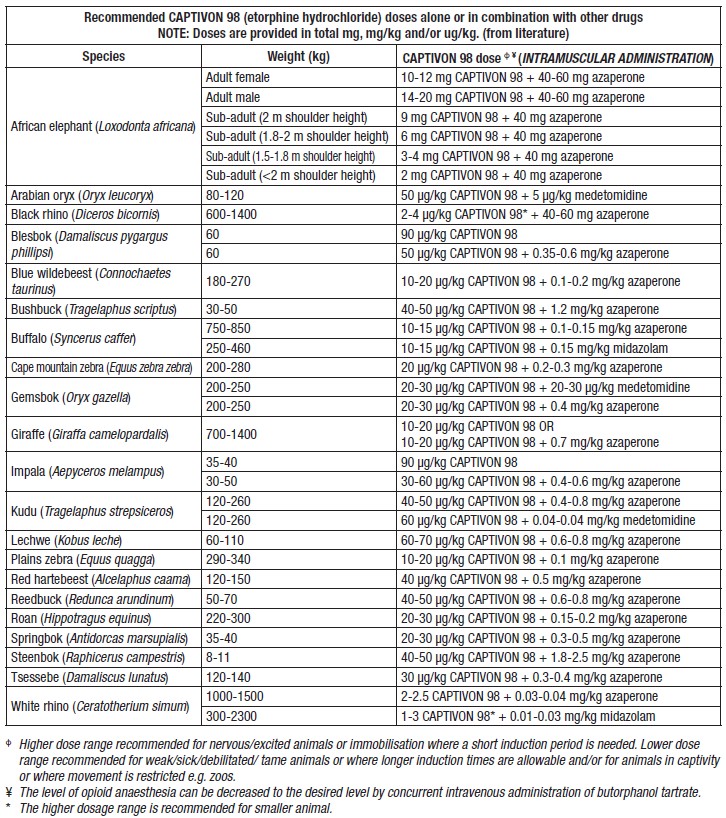 DRUG LABEL: Captivon 98
NDC: 86204-098 | Form: INJECTION, SOLUTION
Manufacturer: Clovis-Davis Pharmaceuticals LLC
Category: animal | Type: PRESCRIPTION ANIMAL DRUG LABEL
Date: 20251215
DEA Schedule: CII

ACTIVE INGREDIENTS: ETORPHINE HYDROCHLORIDE 9.0 mg/1 mL
INACTIVE INGREDIENTS: Chlorocresol; Sodium chloride; WATER

Captivon 98

DESCRIPTION

CII

CAUTION: Federal law restricts this drug to use by or on the order of a licensed veterinarian.

VETERINARY MEDICINE

SCHEDULING STATUS

S6

PROPRIETARY NAME AND DOSAGE FORM

CAPTIVON 98 INJECTION

COMPOSITION

Each ml contains: Etorphine hydrochloride 9.8 mg
Preservative: Chlorocresol 0.1 % m/v

CATEGORY AND CLASS OF MEDICINE

C 1.3.1 Opioid agonist

PHARMACOLOGICAL ACTION

Etorphine is a highly potent, semi-synthetic opioid derivative of oripavine and is classified as a pure agonist. It acts stereospecifically on μ-, δ- and к-opioid receptors, inducing catatonia associated with analgesia at low doses.

PHARMACOKINETIC PROPERTIES AND PHARMACODYNAMIC PROPERTIES

Following intramuscular administration of optimal doses, onset of action in most wildlife species is observed within 2–8 minutes with the full effect reached in 15–30 minutes. In rodents, the analgesic effect peaks sharply at 15 minutes with a duration of action of approximately 50 minutes. In elephants, peak serum concentration is reached 30 minutes after intramuscular injection with a half-life of 66 minutes and clearance of 13.6 ml/min/kg.

Etorphine is primarily eliminated in the bile and excreted in the faeces with some excretion occurring in the urine. Full recovery from the effects of etorphine can take up to 7-8 hours if an opioid antagonist is not administered. Re-cycling of etorphine via enterohepatic circulation or redistribution from adipose depots may lead to re-narcotisation of the animal.

INDICATIONS

CAPTIVON 98 is indicated for immobilisation and anaesthesia of zoo animals, captive wildlife, and free-ranging wildlife species not intended for use as food.

CONTRAINDICATIONS

Do not use CAPTIVON 98 in domestic animals and wild felids.
Do not use carcasses of animals treated with etorphine for human consumption.

CAPTIVON 98 residue studies have not been conducted in wildlife animals and consequently, human and predator consumption of carcasses from animals treated with CAPTIVON 98 is not advisable.

DOSAGE AND DIRECTIONS FOR USE IN ANIMALS

CAPTIVON 98 (etorphine hydrochloride) dosing is dependent on species, body mass and the condition of the wildlife animal being treated, and doses should be adjusted accordingly. Administration by intravenous or intramuscular injection is recommended. Refer to the table for CAPTIVON 98 dosing.

ANALGESIC ANTAGONIST FOR ANIMALS

The effects of CAPTIVON 98 may be reversed by administering naltrexone hydrochloride 50 mg/mL at a ratio of 20 mg of naltrexone hydrochloride for every 1 mg of CAPTIVON 98 used.

SIDE EFFECTS AND SPECIAL PRECAUTIONS FOR USE IN ANIMALS

The most serious adverse effect following CAPTIVON 98 administration is respiratory depression, usually observed within the first five minutes after administration. In cases of severe respiratory depression, CAPTIVON 98 should be reversed as soon as possible, and animals should not remain immobilised for longer than necessary to avoid complications.

The use of CAPTIVON 98 in elderly, diseased, emaciated and highly stressed animals carries a greater degree of risk and precautionary measures should be taken, including maintenance of airways and prevention of hyperthermia.

Equids and rhino:
• CAPTIVON 98 may result in a dramatic rise in blood pressure, tachycardia, hyperpyrexia and pronounced muscle tremors.
• Administration in rhino may lead to hypoventilation, hypoxaemia and metabolic acidosis.

Ungulates
• Significant hypertension due to an increase in total peripheral resistance, and moderate to severe bradycardia has been reported in ungulate species.
• Excitement, increased muscle tone and resulting hyperthermia is particularly common in ungulates.
• Passive regurgitation of rumen contents is common, and ruminants should be kept in sternal recumbency with heads lifted and tilted downwards to prevent aspiration pneumonia.
• Under-dosing may cause hyper-excitability, hyperventilation and severe alkalosis.

The safety of CAPTIVON 98 in pregnant and lactating wildlife animals has not been established. There is a risk of respiratory depression in the newborn if CAPTIVON 98 is given to a parturient animal. Rodent studies have shown that etorphine readily crosses the placental barrier. Etorphine administered in pregnant rats results in respiratory depression in the mother and depressed oxygen uptake in the newborn rats that is directly proportional to the maternal dose.

KNOWN SYMPTOMS OF OVERDOSAGE AND PARTICULARS OF ITS TREATMENT FOR ANIMALS

CAPTIVON 98 toxicity in wildlife animals results in respiratory depression and cardiac suppression. Rhinos are particularly sensitive to CAPTIVON 98.

An overdose can be treated with naltrexone hydrochloride and with analeptics such as doxapram hydrochloride. Oxygen supplementation is recommended in cases of severe respiratory depression. Butorphanol tartrate may be used to partially reverse respiratory depression and to lighten the plane of anaesthesia of large species such as rhino. In the latter case, the animals may be walked under sedation onto vehicles for transport.

HUMAN SAFETY WARNINGS

Accidental exposure to CAPTIVON 98 could have serious effects on humans due to the high concentration of the medicine.
• The lethal CAPTIVON 98 dose in humans is estimated to be between 30-120 μg.

The following precautions should be taken by veterinarians when using CAPTIVON 98:
• Do not work with CAPTIVON 98 unaccompanied.
• Ensure that the antidote (naloxone), and a needle and syringe for administration of the antidote are readily available.
• An assistant capable of administering the antidote to humans should always be present and should be fully briefed on the procedure to follow in the event of accidental exposure to CAPTIVON 98.
• Wear gloves when handling CAPTIVON 98.
• Eye protection should be utilised if there is a risk of CAPTIVON 98 splashing into the eyes.
• Ensure water or an appropriate irrigation solution is available to treat accidental exposure of the skin or eyes.
• CAPTIVON 98 should not be used in blowpipes or similar devices where the medicine solution is pressurised.
• Accidental jabbing with a needle containing CAPTIVON 98 could have serious effects. Once the required dose of CAPTIVON 98 has been withdrawn from the vial, the needle should be immediately discarded into a closed container or sharps bin.

• Symptoms of toxicity in humans include dizziness, nausea, pinpoint pupils, respiratory depression, hypotension, loss of consciousness and cardiac arrest.
• In the event of accidental topical exposure of the skin or eyes, wash the affected area immediately with copious amounts of water to prevent absorption. Monitor for symptoms of toxicity.
• Should accidental injection occur, seek medical attention immediately.

BEFORE CALLING FOR MEDICAL ASSISTANCE, INJECT THE ANTIDOTE.

ADMINISTRATION OF THE ANTIDOTE FOR HUMANS

• Inject 0.8-1.2 mg naloxone preferably IV or alternatively IM and repeat at 2–3 minute intervals until symptoms are reversed. Monitor airway and ventilation and initiate CPR as necessary until medical help arrives.

IDENTIFICATION

A clear, colourless solution for injection.

PRESENTATION

CAPTIVON 98 is supplied in an amber 10 mL glass vial filled to 5 mL.

STORAGE INSTRUCTIONS

Store at or below 25 °C. Protect from light.
Once the rubber stopper has been pierced, the contents of the vial should be used within two weeks.
KEEP OUT OF REACH OF CHILDREN AND UNINFORMED PERSONS.

REGISTRATION NUMBER

93/1.3.1/10

NAME AND BUSINESS ADDRESS OF HOLDER OF CERTIFICATE OF REGISTRATION

Wildlife Pharmaceuticals (Pty) Ltd
38 Wilken Street
Rocky Drift
White River 1240
South Africa

VETERINARY INFORMATION SHEET

CII

CAPTIVON 98
(etorphine hydrochloride)
Injectable Solution
9.8 mg/ml

VETERINARY INFORMATION SHEET

PLEASE READ THIS ENTIRE VETERINARY INFORMATION SHEET
AND THE ENTIRE CAPTIVON 98 PACKAGE INSERT PRIOR TO EACH USE.

CAUTION: Federal law restricts this drug to use by or on the order of a licensed veterinarian.

Do not use this product without adequate amounts of reversal agent available.

WARNINGS: SERIOUS OR LIFE-THREATENING RISKS TO HUMANS FROM ACCIDENTAL EXPOSURE TO CAPTIVON 98

CAPTIVON 98 is a high concentration (9.8 mg/mL) opioid agonist and Schedule II controlled substance. CAPTIVON 98 should be handled with extreme caution to avoid accidental exposure.

Accidental Human Exposure:
Accidental exposure of even one dose of CAPTIVON 98, especially in children, can result in a fatal overdose of etorphine. Strict adherence to the recommended handling and disposal instructions is of utmost importance to prevent accidental exposure.

If accidental self-injection or ingestion occurs, seek immediate medical treatment, and provide physician with the vial or package insert/Veterinary Information Sheet. The reversal agent for human exposure to CAPTIVON 98 is an opioid antagonist such as naloxone or naltrexone.

Symptoms of toxicity include dizziness, nausea, and constriction of pupils (pinpoint) followed by respiratory depression, lowered blood pressure, cyanosis, and in extreme cases, loss of consciousness and cardiac arrest. If necessary, provide airway support, and apply CPR until medical help arrives.

If accidental skin exposure occurs, wash area with copious amounts of water and contact a physician. If accidental eye exposure occurs, flush with copious amounts of water for 15 minutes and contact a physician.

Life-Threatening Respiratory Depression in Humans:
Serious, life-threatening, or fatal respiratory depression may occur with accidental exposure to or with misuse or abuse of CAPTIVON 98. Monitor for respiratory depression if human exposure to CAPTIVON 98 occurs. Misuse or abuse of CAPTIVON 98 by swallowing, snorting, or injecting poses a significant risk of overdose and death.

Abuse Potential in Humans:
CAPTIVON 98 contains etorphine, an opioid that exposes humans to risks of misuse, abuse, and addiction, which can lead to overdose and death. Use of CAPTIVON 98 may lead to physical dependence. The risk of abuse by humans should be considered when storing, administering, and disposing of CAPTIVON 98. Persons at increased risk for opioid abuse include those with a personal or family history of substance abuse (including drugs or alcohol) or mental illness (e.g., depression).

Risks From Concurrent Misuse or Abuse with Benzodiazepines or Other CNS Depressants in Humans:
Concurrent misuse or abuse of opioids with benzodiazepines or other central nervous system (CNS) depressants, including alcohol, may result in profound sedation, respiratory depression, coma, and death.

See Human Safety Warnings for detailed information.

HUMAN SAFETY WARNINGS:

Not for use in humans. Keep this and all medications out of reach of children.
Accidental exposure to CAPTIVON 98, especially in children, can result in a fatal overdose.

Human User Safety while handling CAPTIVON 98:
Because of the potential for adverse reactions associated with accidental exposure, CAPTIVON 98 should only be administered by veterinarians in zoo and wildlife practice, or individuals under such veterinary supervision, trained in the handling of potent opioids.

It is advisable to ONLY handle CAPTIVON 98 when accompanied by another person. Wear gloves. Do not spray, squirt, or spill the drug when filling the syringes. Wash at once with large volumes of water if CAPTIVON 98 comes in contact with eyes, skin, or mucous membranes.

At least two people in the field team should be able to recognize signs of toxicity if accidental exposure occurs. They should be familiar with emergency cardiopulmonary resuscitation procedures plus have FIRST AID KITS containing resuscitation aids available.

Information for Physicians
CAPTIVON 98 is a high concentration opioid agonist. Accidental human exposure may produce severe central nervous system depression resulting in respiratory depression or failure followed by coma and death. Treatment should start immediately by administering an appropriate opiate antagonist, providing airway support, and cardiopulmonary resuscitation techniques.

(See reverse side for animal use information)

INDICATION:
For immobilization and anesthesia of zoo animals, captive wildlife, and free-ranging wildlife species not intended for use as food.
Use only when there is a reasonable certainty that the treated animal will not be consumed by humans or food-producing animals (see CAPTIVON 98 package insert for details).

DOSING AND ADMINISTRATION:
See CAPTIVON 98 package insert for dosing table. Note that dosing of CAPTIVON 98 is provided in micrograms/kg (g/kg) and/or total mg of CAPTIVON 98.

For animal reversal, see ANALGESIC ANTAGONIST FOR ANIMALS section of the CAPTIVON 98 package insert.

CONTRAINDICATIONS:
Do not use CAPTIVON 98 in domestic animals.
Do not use CAPTIVON 98 in feline species.
Do not use CAPTIVON 98 in animals that display clinical signs of disease unless its use is imperative to establish a diagnosis and/or administer therapeutic agents. The effects of CAPTIVON 98 on reproductive performance, pregnancy, and lactation have not been determined.
Do not use CAPTIVON 98 in domestic food-producing animals.
Do not use CAPTIVON 98 thirty (30) days before, or during, the hunting season in free-ranging wild animals that might be used for food. Carcasses of animals treated with CAPTIVON 98 are not to be used for human consumption.

ANIMAL SAFETY WARNINGS:
AN OPIOID ANTAGONIST SUCH AS NALTREXONE HYDROCHLORIDE SHOULD ALWAYS BE DRAWN UP, LABELED, AND READILY ACCESSIBLE TO BE USED AS AN ANIMAL REVERSAL AGENT PRIOR TO DRAWING UP CAPTIVON 98. See CAPTIVON 98 package insert for directions.

All species immobilized with CAPTIVON 98 may show signs of excitement, tachycardia or bradycardia, tachypnea or bradypnea, hypertension or hypotension, depressed respiration, cyanosis, poikilothermia, and reaction to sudden noise. Personnel should be advised of these potential opioid effects and trained to respond appropriately (see CAPTIVON 98 package insert).

CONTACT INFORMATION:
Clovis Davis Pharmaceuticals, LLC
2518 Burnsed Blvd. Ste. 610. The Villages, FL 32163
(313) 466 6469
info@clovisdavis.com
To report suspected adverse drug experiences, contact Wildlife Pharmaceuticals (Pty) Ltd: pharmacist@wildpharm.co.za.
For additional information about reporting adverse drug experiences for animal drugs, contact FDA at 1-888-FDA-VETS (1-888-332-8387) or http://www.fda.gov/reportanimalae.

STORAGE:
CAPTIVON 98 is a Schedule II opioid. Store in a locked cabinet at or below 77 °F (25 °C) according to federal and state-controlled substance requirements/guidelines. Once the vial has been pierced, the contents must be used within two weeks. Protect from light and prolonged exposure to excessive heat. Any unused or expired vials must be destroyed by a reverse distributor. For further information, contact your local DEA field office or email Wildlife Pharmaceuticals (Pty) Ltd: pharmacist@wildpharm.co.za.

CAPTIVON 98 (etorphine hydrochloride) is not FDA approved. Due to a shortage of etorphine hydrochloride in the US, FDA is allowing temporary use of this South African product in the US. CAPTIVON 98 is authorized for marketing in South Africa for the immobilization and anesthesia of zoo animals, captive wildlife, and free-ranging wildlife species not intended for use as food.

NDC NO. 86204-098-05

Wildlife Pharmaceuticals (Pty) Ltd
38 Wilken Street
Rocky Drift
White River 1240, South Africa
+27 13 751 2328

DISTRIBUTED BY
Clovis-Davis Pharmaceuticals, LLC
1520 South Lapeer Rd, Suite 120
Lake Orion, Michigan 48360
833-878-0060

VIAL LABEL

CAPTIVON 98
ETORPHINE HCl 9.8 mg/mL

INJECTABLE SOLUTION

CII
IMMOBILIZATION AGENT
FOR IV / IM USE

WARNING: Due to serious human safety and abuse concerns, read the entire Veterinary Information Sheet and Package Insert before using this drug, including the complete Boxed Warning.

NET CONTENTS: 5 mL NDC: 86204-098-05

Store at or below 25 ºC (77 ºF). Protect from light.
KEEP OUT OF REACH OF CHILDREN AND
UNINFORMED PERSONS.

CAPTIVON 98 (ETORPHINE HCl) is not FDA
approved. Due to a shortage in the USA, the FDA is
allowing temporary use of this South African authorized
product. CAUTION: Federal law restricts
this drug to use by or on the order of a licenced
veterinarian.

Manufactured by: Wildlife Pharmaceuticals
Distributed by: Clovis-Davis Pharmaceuticals, LLC
1520 South Lapeer Rd, Suite 120 Lake Orion, Michigan 48360
833-878-006

CARTON

VETERINARY MEDICINE

CAPTIVON 98
ETORPHINE HCl 9.8 mg/mL
INJECTABLE SOLUTION

CII

WARNING: Due to serious human
safety and abuse concerns, read
the entire Veterinary Information
Sheet and Package Insert before
using this drug, including the
complete Boxed Warning.

Batch:

Exp.:

CAPTIVON 98 (ETORPHINE

HCl) is not FDA approved. Due to a
shortage in the US, the FDA is
allowing temporary use of this
South African-authorized product.

CAUTION: Federal law restricts
this drug to use by or on the order
of a licensed veterinarian.

NDC NO. 86204-098-05

Net contents: 5 mL
Immobilization agent for IV / IM
injection in zoo & wildlife species.

Store at or below 25 °C (77 °F).
Protect from light. KEEP OUT OF
REACH OF CHILDREN AND
UNINFORMED PERSONS.

Once the vial is pierced, contents
must be used within two weeks.

Date first opened: ........................

Because of the potential for adverse
reactions associated with accidental
exposure, CAPTIVON 98 should only be
administered by veterinarians in zoo and
wildlife practice, or individuals under such
veterinary supervision, trained in handling of
potent opioids.

Do not use this product without adequate
amounts of reversal agent available.

Manufactured by:

WILDLIFE PHARMACEUTICALS (Pty)Ltd

38 Wilken Street

Rocky Drift

White River 1240, South Africa

Distributed by:
Clovis-Davis Pharmaceuticals, LLC
1520 South Lapeer Rd, Suite 120
Lake Orion, Michigan 48360
833-878-0060